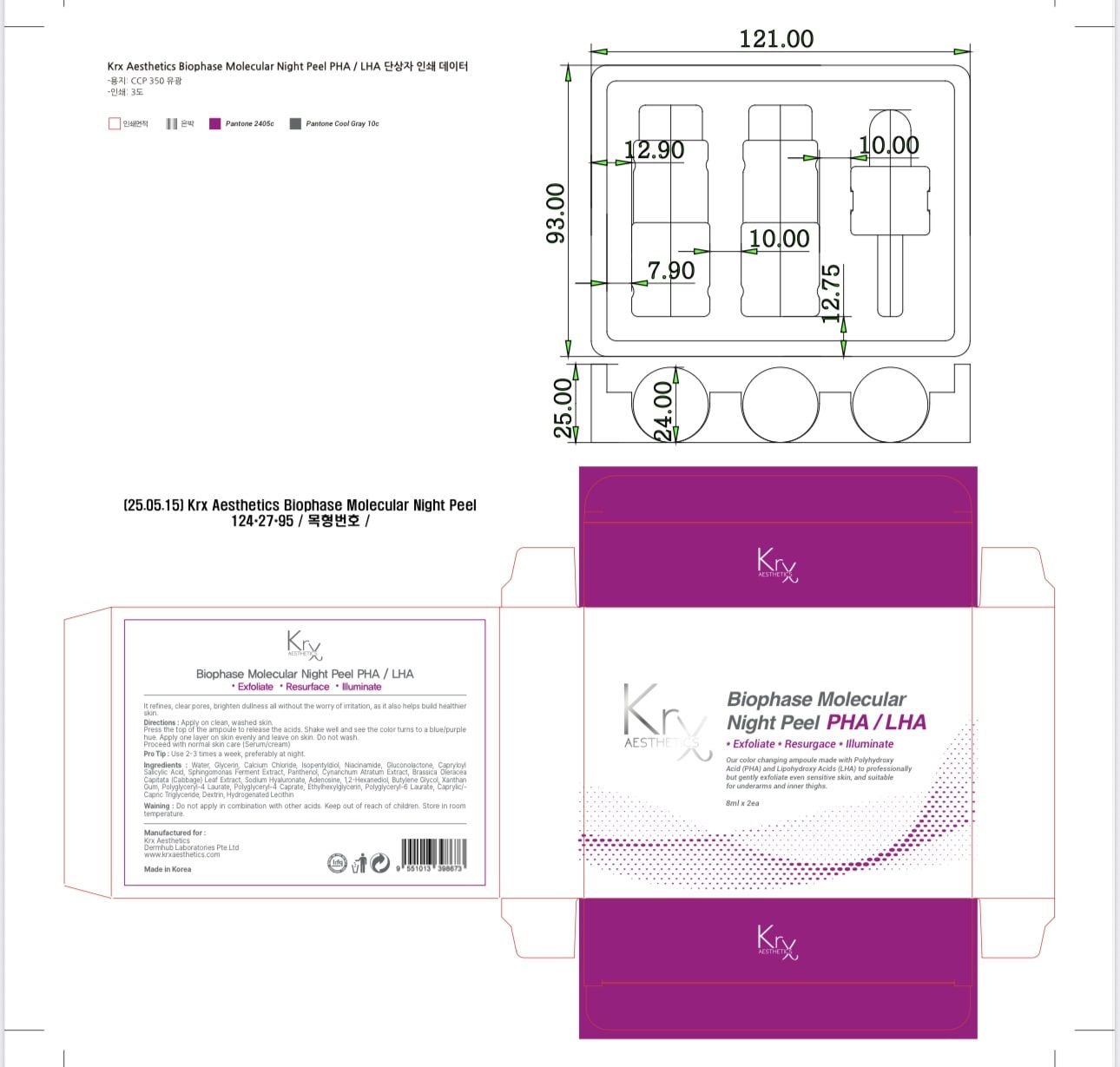 DRUG LABEL: Krx Aesthetics Biophase Molecular Night Peel
NDC: 84755-0005 | Form: CREAM
Manufacturer: KRX RESOURCES SDN. BHD.
Category: otc | Type: HUMAN OTC DRUG LABEL
Date: 20251018

ACTIVE INGREDIENTS: SALICYLOYL PHYTOSPHINGOSINE 10 mg/1 U; GLUCONOLACTONE 100 mg/1 U
INACTIVE INGREDIENTS: BUTYLENE GLYCOL; CAPRYLYL GLYCOL; SODIUM HYALURONATE; NIACINAMIDE; ALLANTOIN; BIOSACCHARIDE GUM-1; DIPROPYLENE GLYCOL; WATER; PANTHENOL; HYDROXYACETOPHENONE; ETHYLHEXYLGLYCERIN; 1,2-HEXANEDIOL; BETAINE; PHENOXYETHANOL; CHLORPHENESIN; PENTYLENE GLYCOL; SODIUM CITRATE

Dosage and Administration

- For topical use only.
- Apply evenly to clean, dry skin at night, avoiding the eye and lip areas.
- Use 1–2 times per week or as directed by a skincare professional.
- Do not rinse off immediately; leave on overnight unless irritation occurs.
- Begin with less frequent use to assess tolerance, especially for sensitive skin.
- Always apply a broad-spectrum sunscreen during the day when using this product.
- Do not apply on broken, inflamed, or compromised skin.

WARNINGS

For external use only.

Avoid contact with eyes and mucous membranes. If contact occurs, rinse thoroughly with water.

Do not apply to broken, irritated, or inflamed skin.

A mild tingling or redness may occur. If severe irritation develops, discontinue use and consult a healthcare professional.

Use sunscreen and limit sun exposure while using this product, as it may increase skin sensitivity to the sun.

Keep out of reach of children. If swallowed, get medical help or contact a Poison Control Center immediately.

INACTIVE INGREDIENT

Water

Butylene Glycol

Niacinamide

Panthenol

Dipropylene Glycol

Pentylene Glycol

Betaine

Sodium Citrate

Hydroxyacetophenone

Allantoin

Biosaccharide Gum-1

Sodium Hyaluronate

Ethylhexylglycerin

Caprylyl Glycol

1,2-Hexanediol

Phenoxyethanol

Chlorphenesin

Fragrance

Indications and Usage

- KrX Aesthetics Biophase Molecular Night Peel (PHA/LHA) is indicated for topical use as an exfoliating treatment.
- Helps gently resurface the skin to improve texture, clarity, and brightness.
- Aids in the removal of dead skin cells while promoting a smoother, more radiant complexion.
- Recommended for use at night as part of a skincare regimen.
- Not intended for use on broken or inflamed skin.

keep out of reach of children

PURPOSE

Exfoliant / Skin Resurfacing

Brightening & Smoothing

ACTIVE INGREDIENT

Gluconolactone (PHA)

Salicyloyl Phytosphingosine (LHA)

PACKAGE LABEL

Product labeling